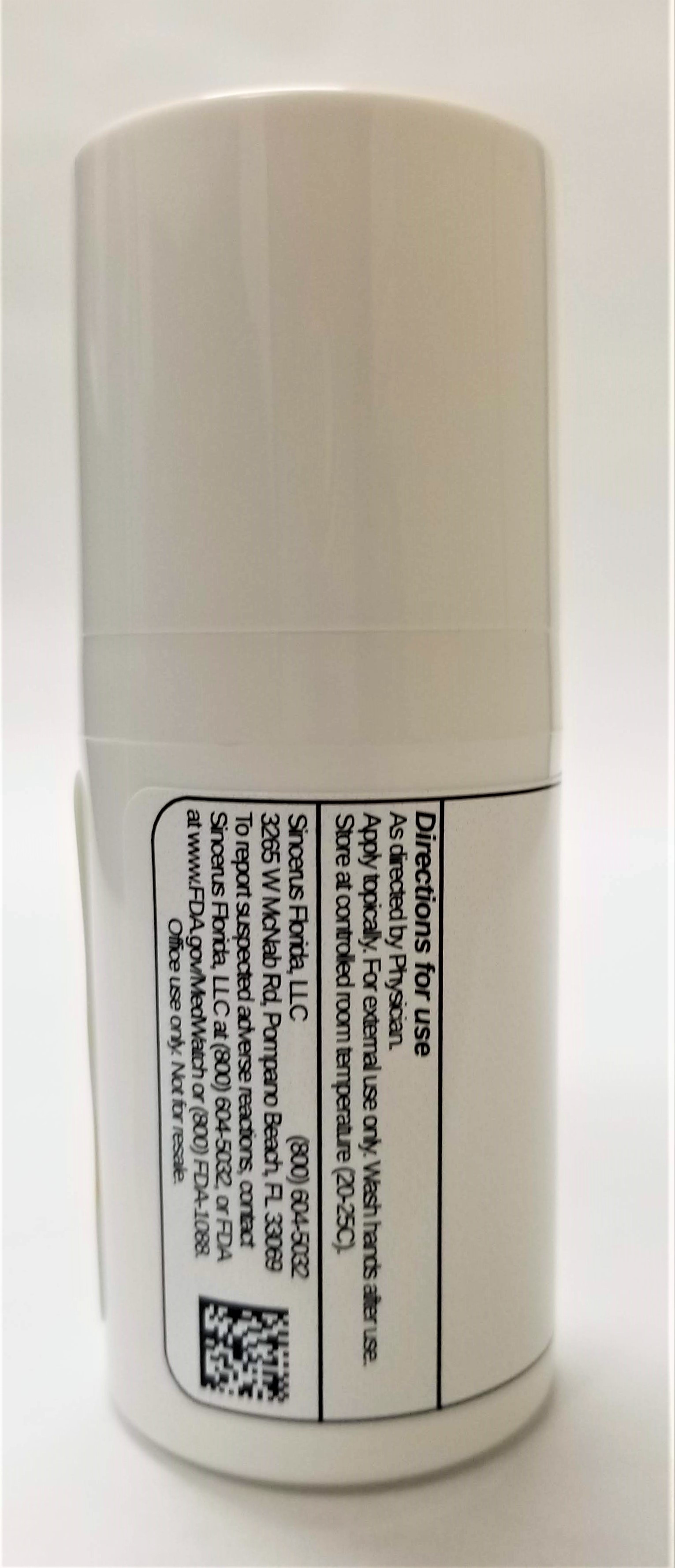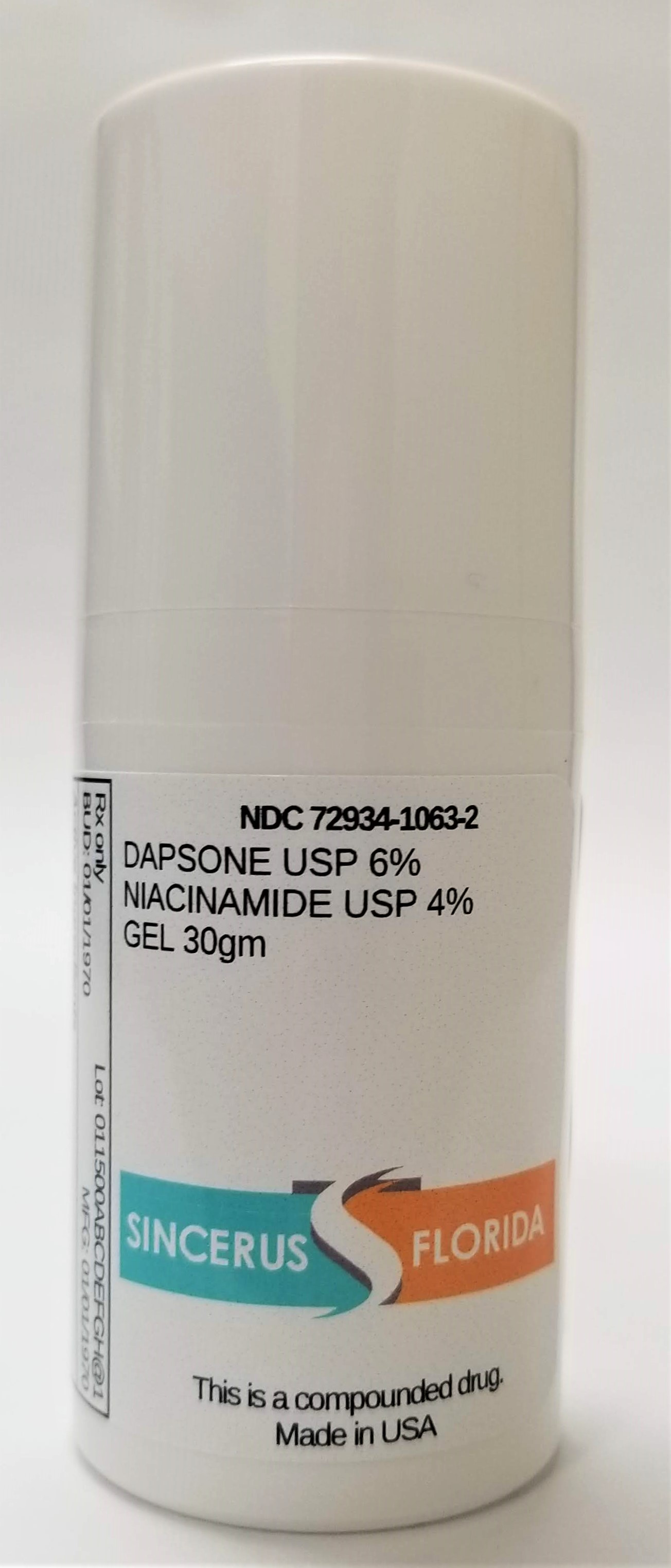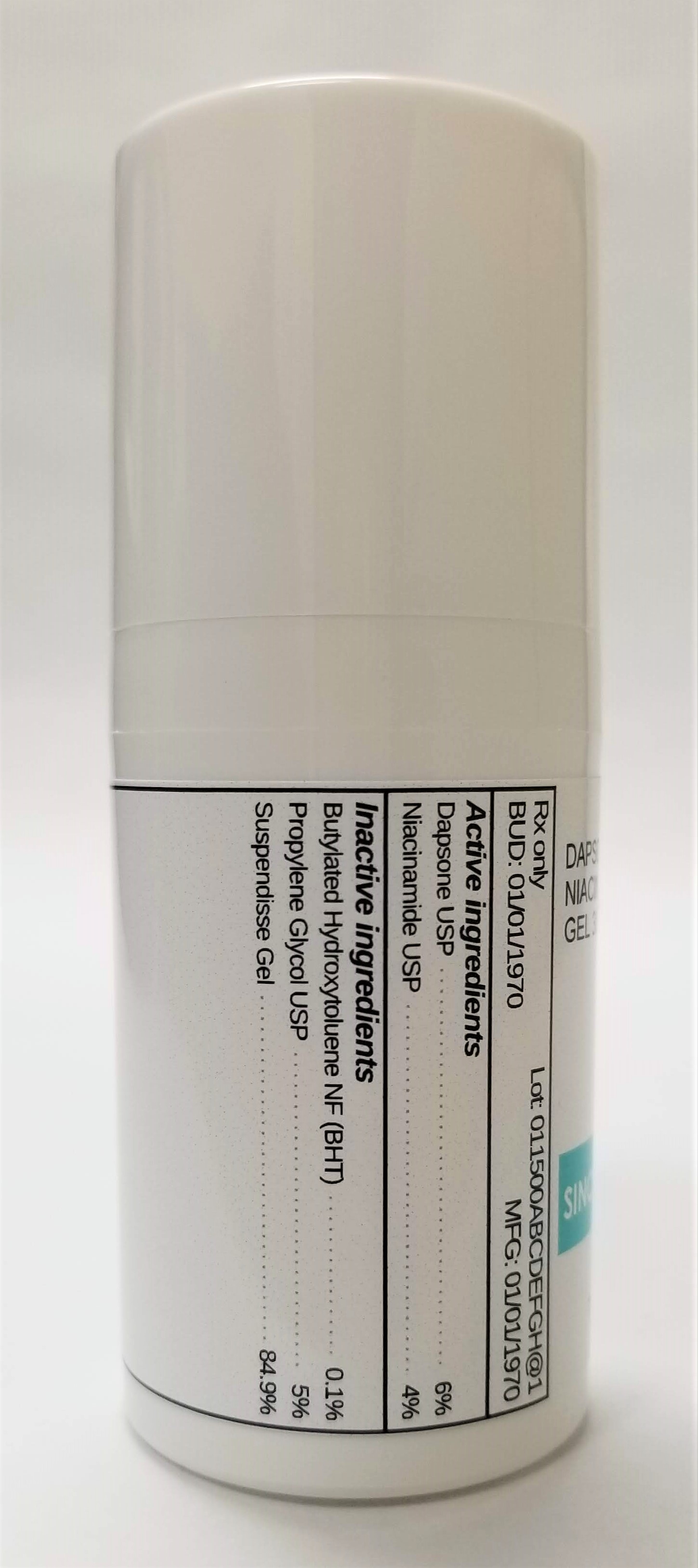 DRUG LABEL: DAPSONE 6% / NIACINAMIDE 4%
NDC: 72934-1063 | Form: GEL
Manufacturer: Sincerus Florida, LLC
Category: prescription | Type: HUMAN PRESCRIPTION DRUG LABEL
Date: 20190423

ACTIVE INGREDIENTS: DAPSONE 6 g/100 g; NIACINAMIDE 4 g/100 g

DAPSONE 6% / NIACINAMIDE 4%